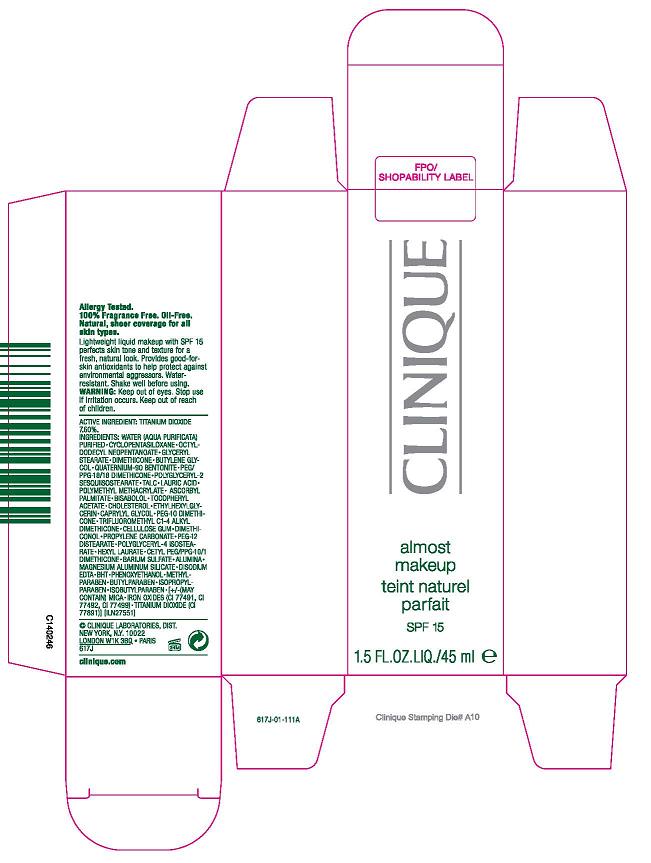 DRUG LABEL: ALMOST MAKEUP
NDC: 49527-002 | Form: LIQUID
Manufacturer: CLINIQUE LABORATORIES INC
Category: otc | Type: HUMAN OTC DRUG LABEL
Date: 20100402

ACTIVE INGREDIENTS: TITANIUM DIOXIDE 45 mL/100 mL

ACTIVE INGREDIENT: TITANIUM DIOXIDE 7.6%

WARNINGS

WARNING: KEEP OUT OF EYES. STOP USE IF IRRITATION OCCURS. KEEP OUT OF REACH OF CHILDREN

PACKAGE LABEL

PRINCIPLE DISPLAY PANEL 0.45 FL OZ CARTON

CLINIQUE

ALMOST MAKEUP
SPF 15

CLINIQUE LABORATORIES DIST.
NEW YORK, NY 10022
617J
CLINIQUE.COM